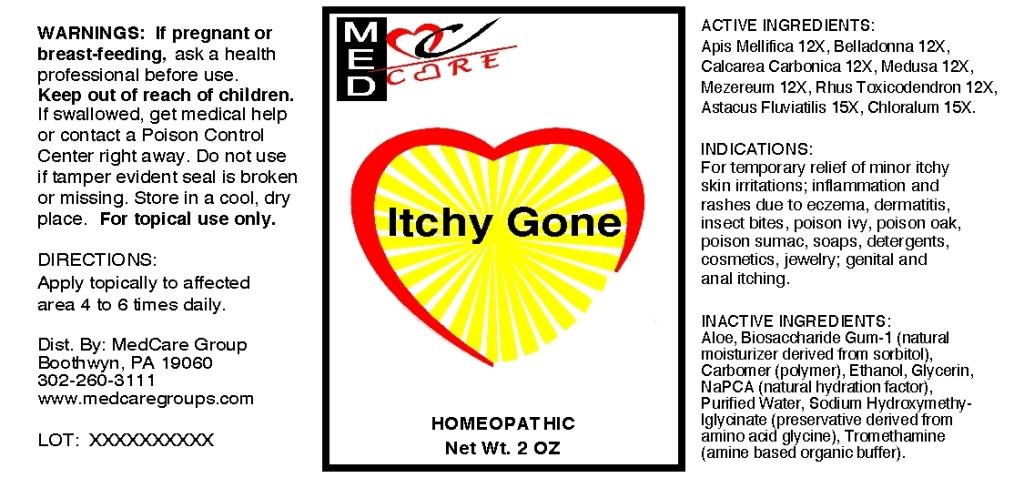 DRUG LABEL: Itchy Gone
NDC: 57520-0777 | Form: GEL
Manufacturer: Apotheca Company
Category: homeopathic | Type: HUMAN OTC DRUG LABEL
Date: 20120126

ACTIVE INGREDIENTS: APIS MELLIFERA 12 [hp_X]/1 g; ATROPA BELLADONNA 12 [hp_X]/1 g; OYSTER SHELL CALCIUM CARBONATE, CRUDE 12 [hp_X]/1 g; DAPHNE MEZEREUM BARK 12 [hp_X]/1 g; TOXICODENDRON PUBESCENS LEAF 12 [hp_X]/1 g; ASTACUS ASTACUS 15 [hp_X]/1 g; CHLORAL HYDRATE 15 [hp_X]/1 g; PHYSALIA PHYSALIS 12 [hp_X]/1 g
INACTIVE INGREDIENTS: ALOE; BIOSACCHARIDE GUM-1; ALCOHOL; GLYCERIN; SODIUM PYRROLIDONE CARBOXYLATE; WATER; SODIUM HYDROXYMETHYLGLYCINATE; TROMETHAMINE; CARBOMER HOMOPOLYMER TYPE C

Itchy Gone

ACTIVE INGREDIENT

ACTIVE INGREDIENTS: Apis mellifica 12X, Belladonna 12X, Calcarea carbonica 12X, Medusa 12X, Mezereum 12X, Rhus toxicodendron 12X, Astacus fluviatilis 15X, Chloralum 15X.

PURPOSE

INDICATIONS: For temporary relief of minor itchy skin irritations; inflammation and rashes due to eczema, dermatitis, insect bites, poison ivy, poison oak, poison sumac, soaps, detergents, cosmetics, jewelry; genital and anal itching.

WARNINGS

WARNINGS: If pregnant or breast-feeding, ask a health professional before use.

Keep out of reach of children. If swallowed, get medical help or contact a Poison Control Center right away.

Do not use if tamper evident seal is broken or missing.

Store in a cool, dry place.

For topical use only.

DOSAGE AND ADMINISTRATION

DIRECTIONS: Apply topically to affected area 4 to 6 times daily.

INACTIVE INGREDIENT

INACTIVE INGREDIENTS: Aloe, Biosaccharide gum-1, Carbomer, Ethanol, Glycerin, NaPCA, Purified water, Sodium hydroxymethylglycinate, Tromethamine.

KEEP OUT OF REACH OF CHILDREN. If swallowed, get medical help or contact Poison Control Center right away.

INDICATIONS AND USAGE

INDICATIONS: For temporary relief of minor itchy skin irritations; inflammation and rashes due to eczema, dermatitis, insect bites, poison ivy, poison oak, poison sumac, soaps, detergents, cosmetics, jewelry; genital and anal itching.

QUESTIONS

Dist. By:

MedCare Group

Boothwyn, PA 19060

302-260-3111

www.medcaregroups.com

PACKAGE LABEL

MEDCARE

Itchy Gone

HOMEOPATHIC

Net Wt. 2 OZ